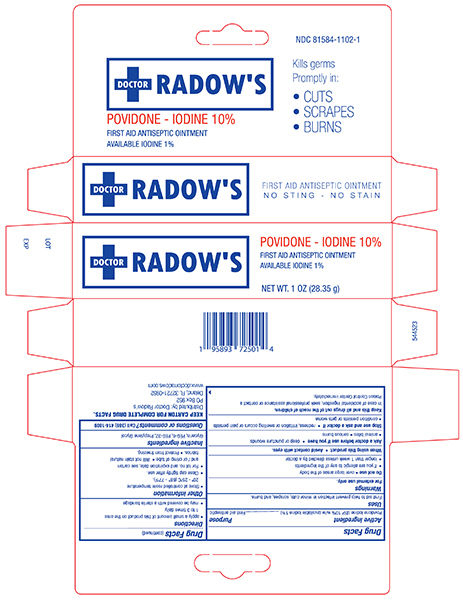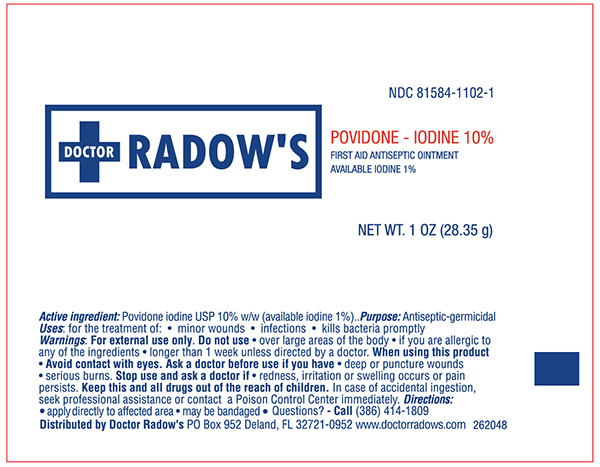 DRUG LABEL: Povidone Iodine
NDC: 81584-1102 | Form: OINTMENT
Manufacturer: Dr Radows
Category: otc | Type: HUMAN OTC DRUG LABEL
Date: 20231030

ACTIVE INGREDIENTS: POVIDONE-IODINE 100 mg/1 g
INACTIVE INGREDIENTS: GLYCERIN; POLYETHYLENE GLYCOL 300; POLYETHYLENE GLYCOL 1500; PROPYLENE GLYCOL

DRUG FACTS

Active ingredient

Povidone Iodine USP10% w/w (available iodine 1%)

Purpose

Antiseptic-germicidal

Uses

for the treatment of:

- minor wounds
- infections
- kills bacteria promptly

Warnings

For external use only.

Do not use

- over large areas of the body
- if you are allergic to any of the ingredients
- longer than 1 week unless directed by a doctor

When using this product

- Avoid contact with eyes.

Ask a doctor before use if you have

- deep or puncture wounds
- animal bites
- serious burns

Stop use and ask a doctor if

- redness, irritation or swelling occurs or pain persists

Keep this and all drugs out of the reach of children.

In case of accidental ingestion, seek professional assistance or contact a Poison Control Center immediately.

Directions

- apply directly to affected area
- may be bandaged

Other information

- Store at controlled room temperature 15°-30°C (59°-86°F).
- Close cap tightly after use.
- For control no. and expiration date, see carton and/or crimp of tube.
- Will not stain natural fabrics.
- Protect from freezing.

Inactive ingredients

glycerin, PEG-6, PEG-32, propylene glycol

Questions?

call (386) 414- 1809

Distributed by Dr Radow's PO Box 952 Deland FL, 32721-0952

Principal Display Panel – 1 oz. Tube

Doctor Radow NDC 81584-1102-1

POVIDINE – IODINE 10%

First Aid Antiseptic Ointment

AVAILABLE IODINE 1%

NET WT. 1 OZ (28.35 g)

Principal Display Panel – 1 oz. Carton

Doctor Radow NDC 81584-1102-1

Povidone Iodine 10%

First Aid Antiseptic Ointment

Available Iodine 1%

NET WT 1 OZ (28.35g)